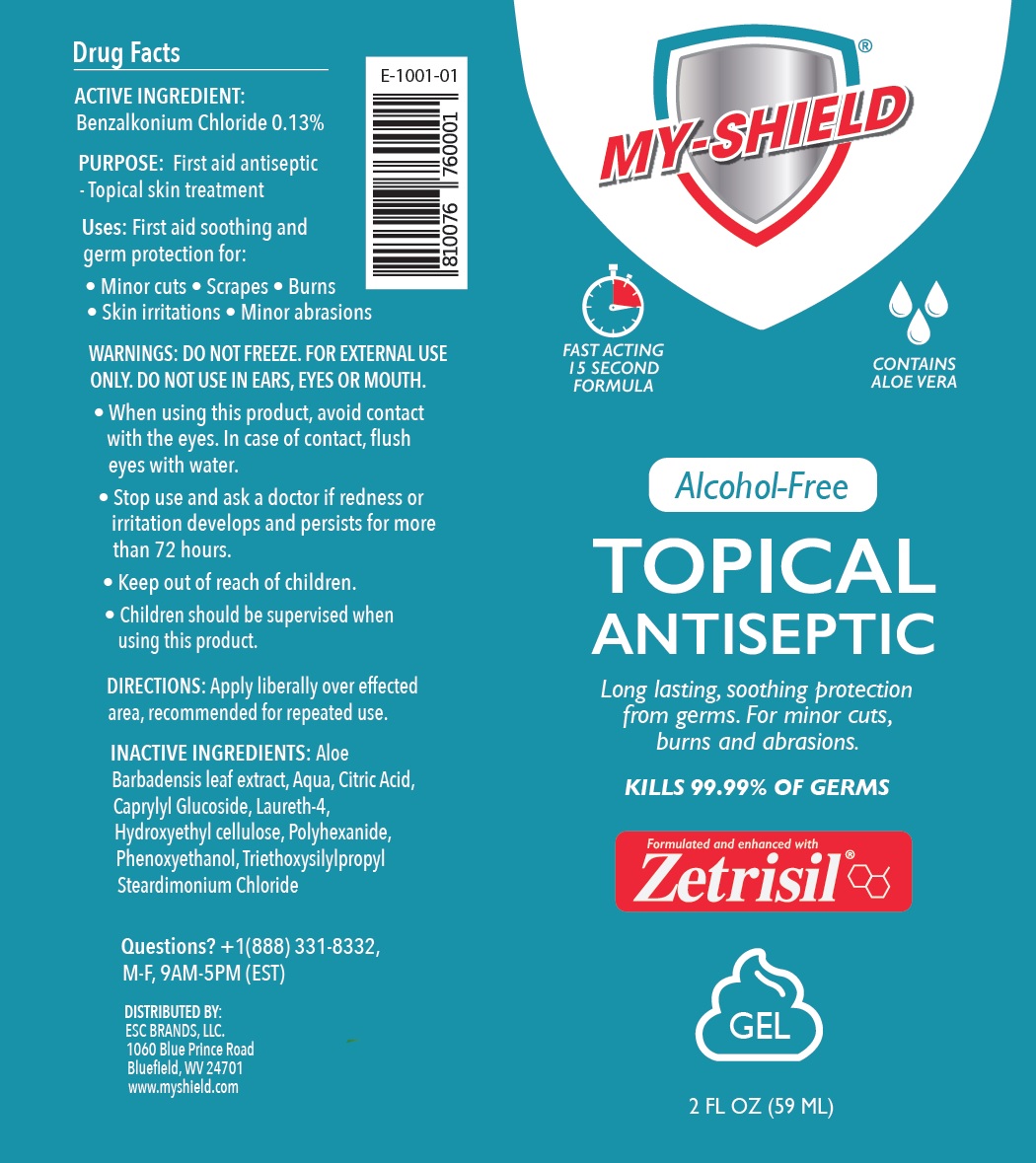 DRUG LABEL: MY-SHIELD TOPICAL ANTISEPTIC
NDC: 71884-025 | Form: GEL
Manufacturer: Enviro Specialty Chemicals Inc
Category: otc | Type: HUMAN OTC DRUG LABEL
Date: 20241231

ACTIVE INGREDIENTS: BENZALKONIUM CHLORIDE 1.3 mg/1 mL
INACTIVE INGREDIENTS: ALOE VERA LEAF; WATER; CITRIC ACID MONOHYDRATE; CAPRYLYL GLUCOSIDE; LAURETH-4; HYDROXYETHYL CELLULOSE, UNSPECIFIED; POLIHEXANIDE; PHENOXYETHANOL; TRIETHOXYSILYLPROPYL STEARDIMONIUM CHLORIDE

MY-SHIELD® TOPICAL ANTISEPTIC

ACTIVE INGREDIENT:

Benzalkonium Chloride 0.13%

PURPOSE:

First aid antiseptic - Topical skin treatment

Uses:

First aid soothing and germ protection for:
• Minor cuts • Scrapes • Burns
• Skin irritations • Minor abrasions

WARNINGS:

DO NOT FREEZE. FOR EXTERNAL USE ONLY. DO NOT USE IN EARS, EYES OR MOUTH.

• When using this product, avoid contact with the eyes. In case of contact, flush eyes with water.

• Stop use and ask a doctor if redness or irritation develops and persists for more than 72 hours.

• Keep out of reach of children.

• Children should be supervised when using this product.

DIRECTIONS:

Apply liberally over affected area, recommended for repeated use.

INACTIVE INGREDIENTS:

Aloe Barbadensis leaf extract, Aqua, Citric Acid, Caprylyl Glucoside, Laureth-4, Hydroxyethyl cellulose, Polyhexanide, Phenoxyethanol, Triethoxysilylpropyl Steardimonium Chloride

Questions?

+1(888) 331-8332, M-F, 9AM-5PM (EST)

FAST ACTING 15 SECOND FORMULA

CONTAINS ALOE VERA

Alcohol-Free

Long lasting, soothing protection from germs.

KILLS 99.99% OF GERMS

Formulated and enhanced with Zetrisil®

DISTRIBUTED BY:
ESC BRANDS, LLC.
1060 Blue Prince Road
Bluefield, WV 24701
www.myshield.com